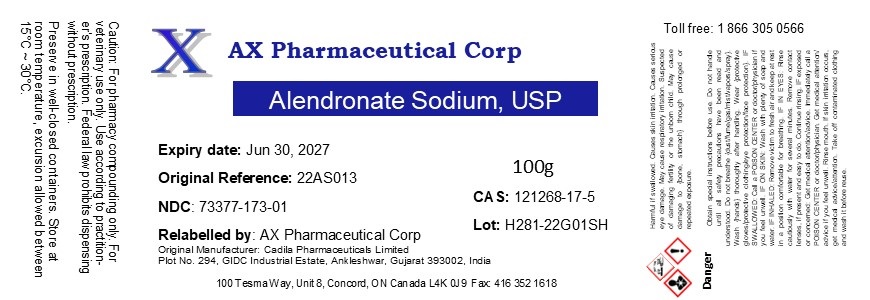 DRUG LABEL: Alendronate Sodium
NDC: 73377-173 | Form: POWDER
Manufacturer: AX Pharmaceutical Corp
Category: other | Type: BULK INGREDIENT - ANIMAL DRUG
Date: 20221109

ACTIVE INGREDIENTS: ALENDRONATE SODIUM 1 g/1 g

Alendronate Sodium